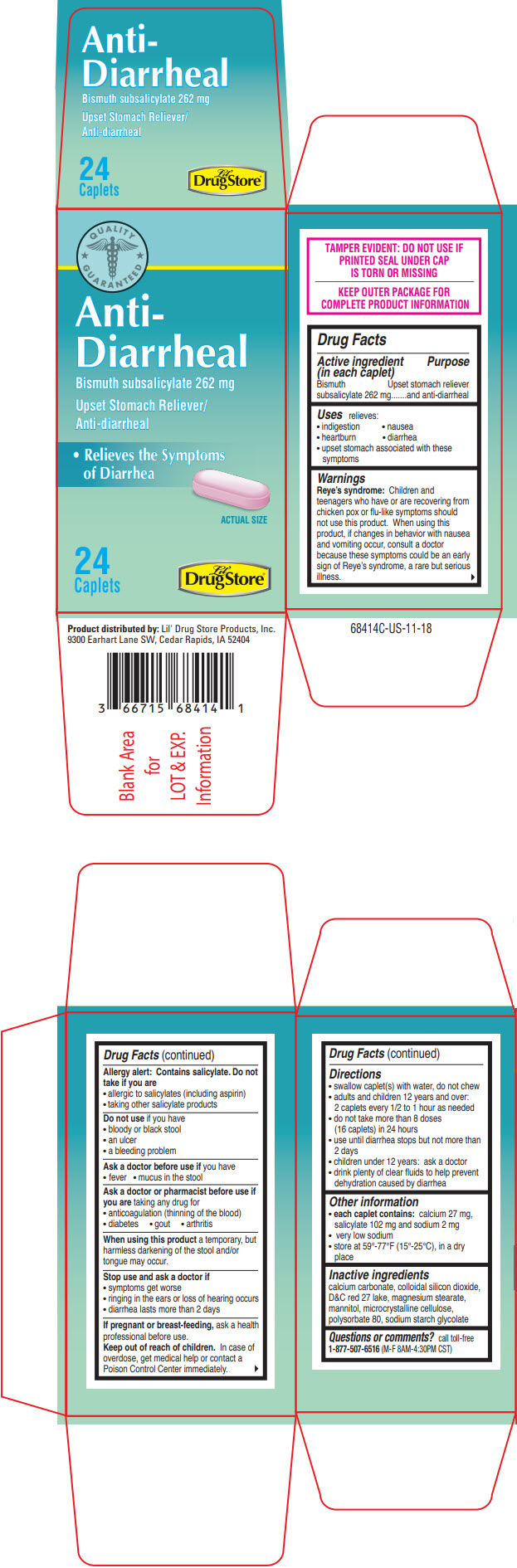 DRUG LABEL: Anti-Diarrheal
NDC: 66715-6841 | Form: TABLET
Manufacturer: Lil' Drug Store Products, Inc.
Category: otc | Type: HUMAN OTC DRUG LABEL
Date: 20241125

ACTIVE INGREDIENTS: BISMUTH SUBSALICYLATE 262 mg/1 1
INACTIVE INGREDIENTS: CALCIUM CARBONATE; SILICON DIOXIDE; D&C RED NO. 27; ALUMINUM OXIDE; MAGNESIUM STEARATE; MANNITOL; MICROCRYSTALLINE CELLULOSE; POLYSORBATE 80; SODIUM STARCH GLYCOLATE TYPE A CORN

Anti-Diarrheal

Drug Facts

Active ingredient (in each caplet)

Bismuth subsalicylate 262 mg

Purpose

Upset stomach reliever and anti-diarrheal

Uses

relieves:

- indigestion
- nausea
- heartburn
- diarrhea
- upset stomach associated with these symptoms

Warnings

Reye's syndrome

Children and teenagers who have or are recovering from chicken pox or flu-like symptoms should not use this product. When using this product, if changes in behavior with nausea and vomiting occur, consult a doctor because these symptoms could be an early sign of Reye's syndrome, a rare but serious illness.

Allergy alert

Contains salicylate. Do not take if you are

- allergic to salicylates (including aspirin)
- taking other salicylate products

Do not use if you have

- bloody or black stool
- an ulcer
- a bleeding problem

Ask a doctor before use if you have

- fever
- mucus in the stool

Ask a doctor or pharmacist before use if you are taking any drug for

- anticoagulation (thinning of the blood)
- diabetes
- gout
- arthritis

When using this product a temporary, but harmless darkening of the stool and/or tongue may occur.

Stop use and ask a doctor if

- symptoms get worse
- ringing in the ears or loss of hearing occurs
- diarrhea lasts more than 2 days

PREGNANCY OR BREAST FEEDING

If pregnant or breast-feeding, ask a health professional before use.

Keep out of reach of children. In case of overdose, get medical help or contact a Poison Control Center immediately.

Directions

- swallow caplet(s) with water, do not chew
- adults and children 12 years and over: 2 caplets every 1/2 to 1 hour as needed
- do not take more than 8 doses (16 caplets) in 24 hours
- use until diarrhea stops but not more than 2 days
- children under 12 years: ask a doctor
- drink plenty of clear fluids to help prevent dehydration caused by diarrhea

Other information

- each caplet contains: calcium 27 mg, salicylate 102 mg and sodium 2 mg
- very low sodium
- store at 59°-77°F (15°-25°C), in a dry place

Inactive ingredients

calcium carbonate, colloidal silicon dioxide, D&C red 27 lake, magnesium stearate, mannitol, microcrystalline cellulose, polysorbate 80, sodium starch glycolate

Questions or comments?

call toll-free 1-877-507-6516 (M-F 8AM-4:30PM CST)

Product distributed by: Lil' Drug Store Products, Inc.
9300 Earhart Lane SW, Cedar Rapids, IA 52404

PRINCIPAL DISPLAY PANEL - 262 mg Caplet Bottle Carton

QUALITY
⋆ GUARANTEED ⋆

Anti-
Diarrheal

Bismuth subsalicylate 262 mg

Upset Stomach Reliever/
Anti-diarrheal

- Relieves the Symptoms
  of Diarrhea

ACTUAL SIZE

24
Caplets

Lil'
Drug Store®